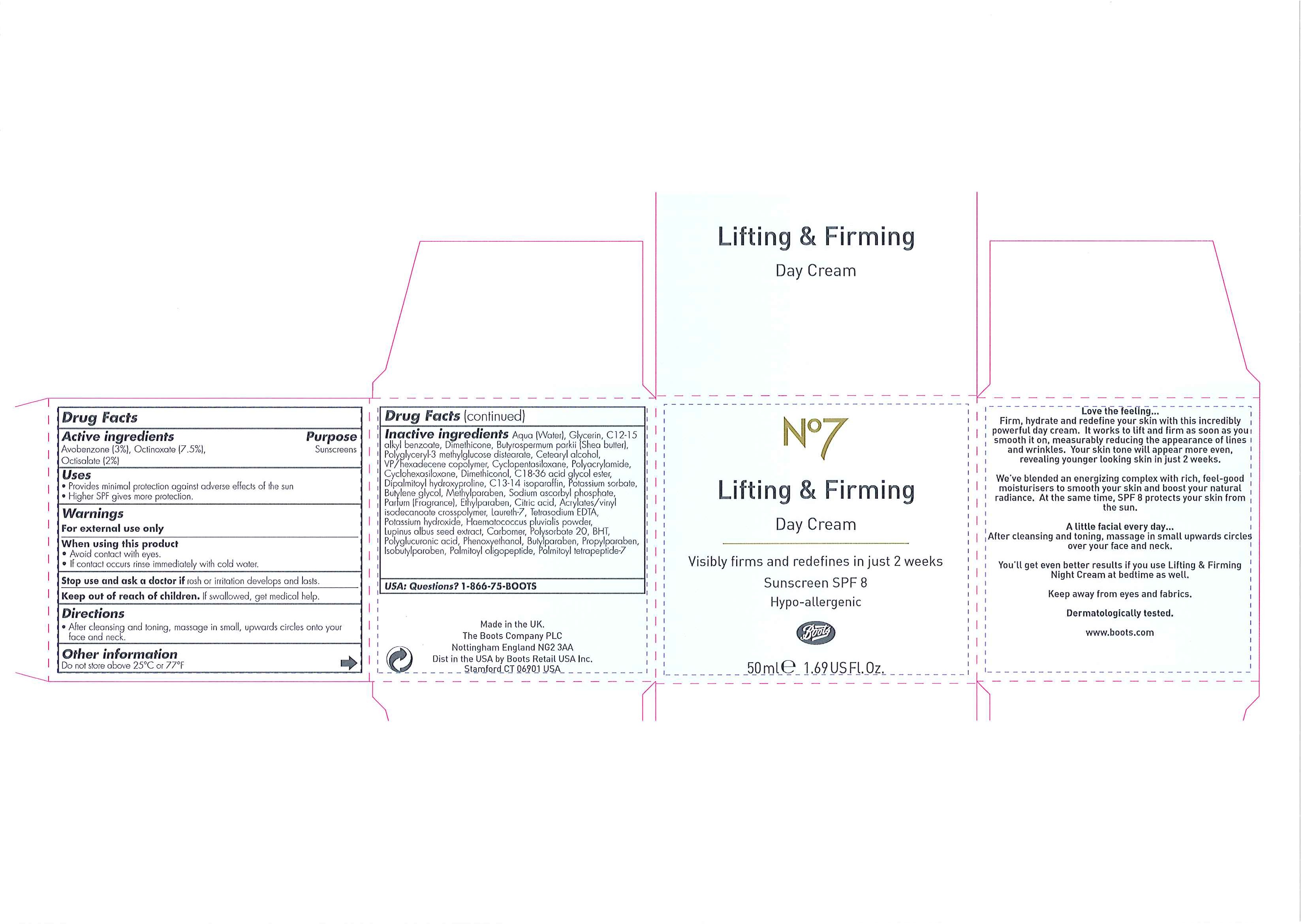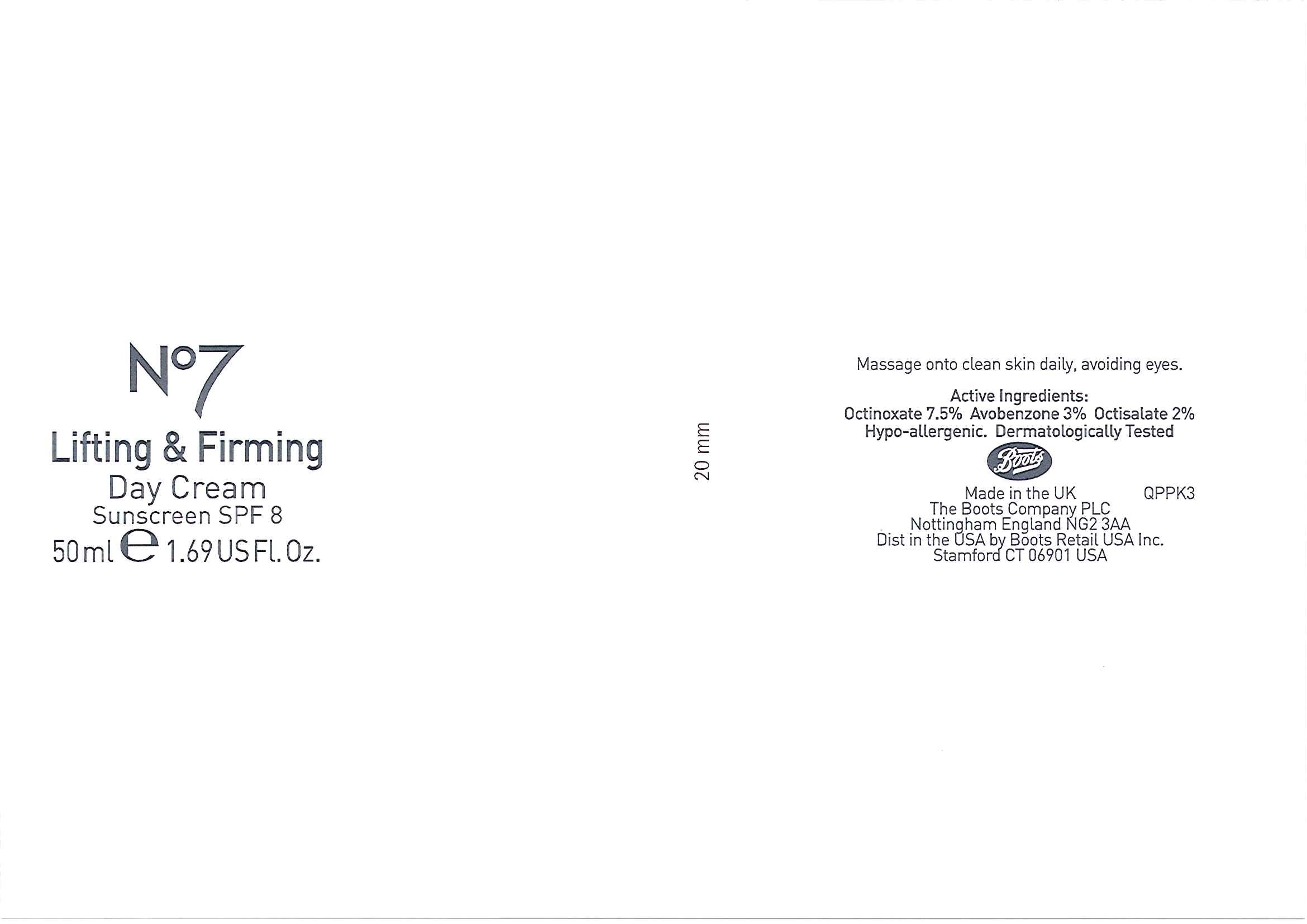 DRUG LABEL: No7 Lifting and Firming Day Sunscreen SPF 8
NDC: 11489-064 | Form: EMULSION
Manufacturer: BCM Ltd
Category: otc | Type: HUMAN OTC DRUG LABEL
Date: 20101206

ACTIVE INGREDIENTS: OCTINOXATE 3.75 mL/50 mL; AVOBENZONE 1.5 mL/50 mL; OCTISALATE 1 mL/50 mL
INACTIVE INGREDIENTS: WATER; GLYCERIN; DIMETHICONE; SHEA BUTTER; CETOSTEARYL ALCOHOL; CYCLOMETHICONE 5; CYCLOMETHICONE 6; POTASSIUM SORBATE; BUTYLENE GLYCOL; METHYLPARABEN; SODIUM ASCORBYL PHOSPHATE; ETHYLPARABEN; CITRIC ACID MONOHYDRATE; POTASSIUM HYDROXIDE; CARBOMER HOMOPOLYMER TYPE C; POLYSORBATE 20; BUTYLATED HYDROXYTOLUENE; PHENOXYETHANOL; BUTYLPARABEN; PROPYLPARABEN; ISOBUTYLPARABEN

Carton and jar labelling

ACTIVE INGREDIENT

No7 Lifting and Firming Day Cream Sunscreen SPF 8

Active ingredients Purpose

Avobenzone (3.0%) Sunscreens

Octinoxate (7.5%)

Octisalate (2.0%)

Uses

- Provides minimal protection against adverse effects of the sun
- Higher SPF gives more protection

Warnings

For external use only

When using this product

- Avoid contact with eyes.
- If contact occurs, rinse immediately with cold water.

Stop use and ask a doctor if rash or irritation develops and lasts.

Keep out of reach of children. If swallowed get medical help.

Directions

- After cleansing and toning, massage in small upwards circles onto your face and neck.

Other information

Do not store above 25^0C or 77^0F

Inactive ingredients

Aqua (Water), Glycerin, C12-15 alkyl benzoate, Dimethicone, Butyrospermum parkii (Shea butter), Polyglyceryl-3 methylglucose distearate, Cetearyl alcohol, VP/hexadecene copolymer, Cyclopentasiloxane, Polyacrylamide, Cyclohexasiloxane, Dimethiconol, C18-36 acid glycol ester, Dipalmitoyl hydroxyproline, C13-14 isoparaffin, Potassium sorbate, Butylene glycol, Methylparaben, Sodium ascorbyl phosphate, Parfum (Fragrance), Ethylparaben, Citric acid, Acrylates/vinyl isodecanoate crosspolymer, Laureth-7, Tetrasodium EDTA, Potassium hydroxide, Haematococcus pluvialis powder, Lupinus albus seed extract, Carbomer, Polysorbate 20, BHT, Polyglucuronic acid, Phenoxyethanol, Butylparaben, Propylparaben, Isobutylparaben, Palmitoyl oligopeptide, Palmitoyl tetrapeptide-7

USA: Questions? 1-866-75-BOOTS

PATIENT COUNSELING INFORMATION

Made in the UK
The Boots Company PLC Nottingham England NG2 3AA
Dist in the USA by Boots Retail USA Inc. Stamford CT 06901 USA

DESCRIPTION

Love the feeling...
Firm, hydrate and redefine your skin with this incredibly powerful day cream. It works to lift and firm as soon as you smooth it on, measurably reducing the appearance of lines and wrinkles. Your skin tone will appear more even, revealing younger looking skin in just 2 weeks.
We've blended an energizing complex with rich, feel-good moisturisers to smooth your skin and boost your natural radiance. At the same time, SPF 8 protects your skin from the sun.
A little facial every day...
After cleansing and toning, massage in small upwards circles over your face and neck.
You'll get even better results if you use Lifting and Firming Night Cream at bedtime as well.
Keep away from eyes and fabrics.
Dermatologically tested.
www.boots.com

DESCRIPTION

Jar label
Massage onto clean skin daily, avoiding eyes.
Hypo-allergenic.
Dermatologically Tested

Active Ingredients:

Octinoxate 7.5%

Avobenzone 3%

Octisalate 2%

PATIENT COUNSELING INFORMATION

Made in the UK

The Boots Company PLC Nottingham England NG2 3AA

Dist in the USA by Boots Retail USA Inc. Stamford CT 06901 USA

Carton label

No7 Lifting and Firming Day Cream

Visibly firms and redefines in just 2 weeks

Sunscreen SPF 8

Hypo-allergenic

Boots

50ml e 1.69 US Fl. Oz

Lifting and Firming Day Cream carton.jpg

PACKAGE LABEL

No7 Lifting and Firming Day Cream

Sunscreen SPF 8

50ml 1.69 US Fl. Oz

Lifting and Firming Day Cream labels.jpg